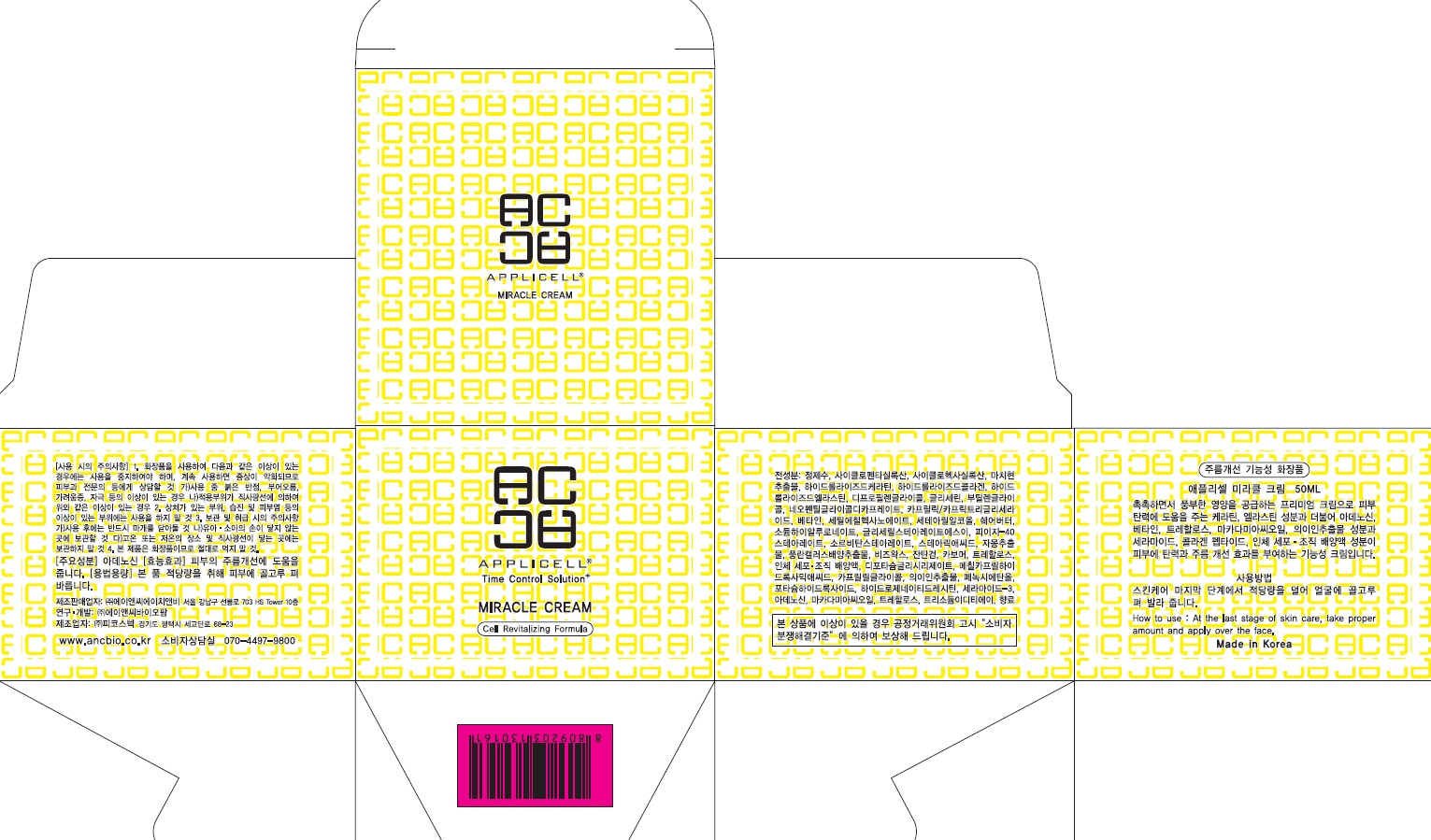 DRUG LABEL: Applicell Miracle
NDC: 71098-040 | Form: CREAM
Manufacturer: Anc HnB Inc.
Category: otc | Type: HUMAN OTC DRUG LABEL
Date: 20161125

ACTIVE INGREDIENTS: Adenosine 0.02 g/50 mL
INACTIVE INGREDIENTS: Water; Dipropylene Glycol

ACTIVE INGREDIENT

Active Ingredient: Adenosine 0.04%

INACTIVE INGREDIENT

Inactive Ingredients: Water, Cyclopentasiloxane, Cyclohexasiloxane, Portulaca Oleracea Extract, Hydrolyzed Keratin, Hydrolyzed Collagen, Hydrolyzed Elastin, Dipropylene Glycol, Glycerin, Butylene Glycol, Neopentyl Glycol Dicaprate, Caprylic/Capric Triglyceride, Betaine, Cetyl Ethylhexanoate, Cetearyl Alcohol, Butyrospermum Parkii(Shea Butter), Sodium Hyaluronate, Glyceryl Stearate SE, PEG-40 Stearate, Sorbitan Stearate, Stearic Acid, Citrus Paradisi (Grapefruit) Fruit Extract, Neofinetia Falcata Callus Culture Extract, Beeswax, Xanthan Gum, Carbomer, Trehalose, Human fibroblast Conditioned Media, Dipotassium Glycyrrhizate , Caprylhydroxamic Acid, Caprylyl Glycol, Coix Lacryma-Jobi Ma-yuen Seed Extract, Phenoxyethanol, Potassium Hydroxide, Hydrogenated Lecithin, Ceramide 3, Macadamia Ternifolia Seed Oil, Trehalose, Trisodium EDTA, Fragrance

PURPOSE

Purpose: Skin Protectant

WARNINGS

Warnings: For external use only When using this product do not get into eyes, Stop use and ask a doctor if rash occurs Do not use on - deep puncture wounds - animal bites - serious burns Keep out of reach of children

KEEP OUT OF REACH OF CHILDREN

INDICATIONS & USAGE

Indications & usage: APPLICELL Miracle Cream is premium cream to supply abundant nutrition in skin and improve skin wrinkle.

DOSAGE & ADMINISTRATION

How to use: At the last stage of skin care, take proper amount and apply over the face.